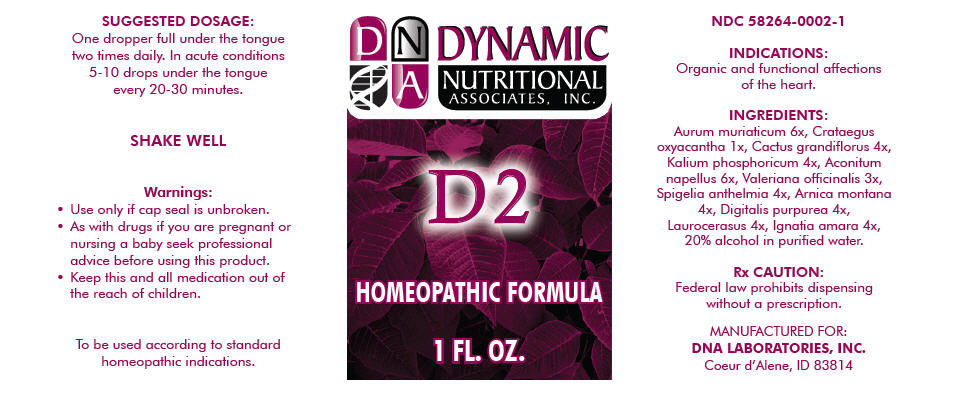 DRUG LABEL: D2
NDC: 58264-0002 | Form: SOLUTION
Manufacturer: DNA Labs, Inc.
Category: homeopathic | Type: HUMAN OTC DRUG LABEL
Date: 20180131

ACTIVE INGREDIENTS: GOLD TRICHLORIDE 6 [hp_X]/1 mL; CRATAEGUS LAEVIGATA WHOLE 1 [hp_X]/1 mL; SELENICEREUS GRANDIFLORUS WHOLE 4 [hp_X]/1 mL; DIBASIC POTASSIUM PHOSPHATE 4 [hp_X]/1 mL; ACONITUM NAPELLUS 6 [hp_X]/1 mL; VALERIANA OFFICINALIS WHOLE 3 [hp_X]/1 mL; SPIGELIA ANTHELMIA 4 [hp_X]/1 mL; ARNICA MONTANA 4 [hp_X]/1 mL; DIGITALIS PURPUREA WHOLE 4 [hp_X]/1 mL; PRUNUS LAUROCERASUS WHOLE 4 [hp_X]/1 mL; STRYCHNOS IGNATII WHOLE 4 [hp_X]/1 mL
INACTIVE INGREDIENTS: Alcohol; Water

D2

NDC 58264-0002-1

INDICATIONS AND USAGE

INDICATIONS

Organic and functional affections of the heart.

ACTIVE INGREDIENT

INGREDIENTS

Aurum muriaticum 6x, Crataegus oxyacantha 1x, Cactus grandiflorus 4x, Kalium phosphoricum 4x, Aconitum napellus 6x, Valeriana officinalis 3x, Spigelia anthelmia 4x, Arnica montana 4x, Digitalis purpurea 4x, Laurocerasus 4x, Ignatia amara 4x, 20% alcohol in purified water.

Rx CAUTION

Federal law prohibits dispensing without a prescription.

SUGGESTED DOSAGE

One dropper full under the tongue two times daily. In acute conditions 5-10 drops under the tongue every 20-30 minutes.

STORAGE AND HANDLING

SHAKE WELL

Warnings

- Use only if cap seal is unbroken.

PREGNANCY OR BREAST FEEDING

- As with drugs if you are pregnant or nursing a baby seek professional advice before using this product.

KEEP OUT OF REACH OF CHILDREN

- Keep this and all medication out of the reach of children.

To be used according to standard homeopathic indications.

PRINCIPAL DISPLAY PANEL - 1 FL. OZ. Bottle Label

DYNAMIC
NUTRITIONAL
ASSOCIATES, INC.

D2

HOMEOPATHIC FORMULA

1 FL. OZ.